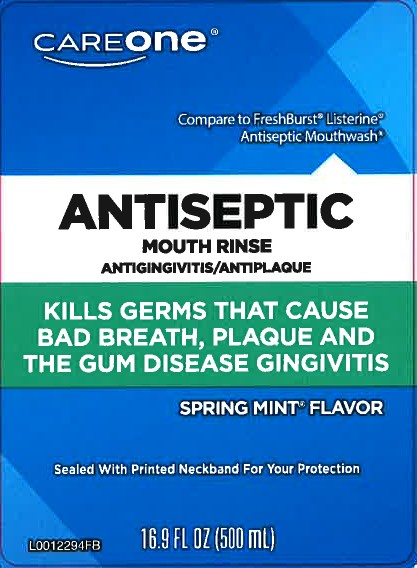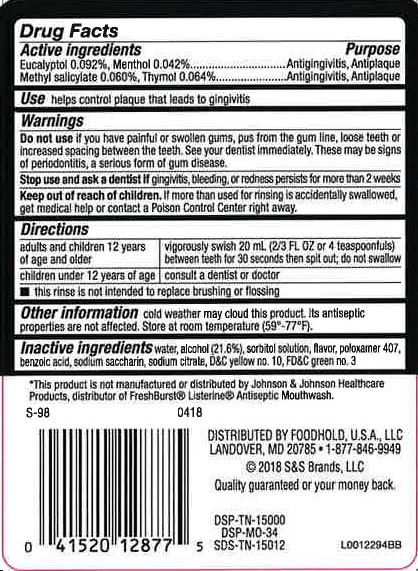 DRUG LABEL: Antiseptic Mouthrinse
NDC: 72476-072 | Form: MOUTHWASH
Manufacturer: Retail Business Services, LLC
Category: otc | Type: HUMAN OTC DRUG LABEL
Date: 20260206

ACTIVE INGREDIENTS: EUCALYPTOL 0.92 mg/1 mL; MENTHOL 0.42 mg/1 mL; METHYL SALICYLATE 0.6 mg/1 mL; THYMOL 0.64 mg/1 mL
INACTIVE INGREDIENTS: ALCOHOL; SORBITOL; POLOXAMER 407; BENZOIC ACID; SACCHARIN SODIUM; SODIUM CITRATE; D&C YELLOW NO. 10; FD&C GREEN NO. 3; WATER

Care One 072.002/072AN
Antiseptic Mouthwash 072.002/072AN

Active ingredients

Eucalyptol 0.092%

Menthol 0.042%

Methyl sailcylate 0.060%

Thymol 0.064%

Purpose

Antigingivitis, Antiplaque

Use

helps control plaque that leads to gingivitis

Warnings

For this product

Do not use if

you have painful or swollen gums, pus from the gum line, loose teeth or increased spacing between the teeth. See your dentist immediately. These may be signs of periodontitis, a serious form of gum disease.

Stop use and ask a dentist if

gingivitis, bleeding, or rednss persists for more than 2 weeks

Keep out of reach of children.

If more than used for rinsing is accidentally swallowed, get medical help or contact a Poison Control Center right away.

Directions

adults and children under 12 years if age and older - vigorously swish 20 ml (2/3 FL OZ or 4 teaspoonfuls) between teeth for 30 seconds then spit out; do not swallow

children under 12 years of age - consult a dentist or doctor

- this rinse is not intended to replace brushing or flossing

Other information

cold weather may cloud this product. Its antiseptic propeties are not affected. Store at room temperature (59° -77° F).

Inactive ingredients

water, alcohol (21.6 %), sorbitol solution, flavor, poloxamer 407, benzoic acid, sodium saccharin, sodium citrate, D&C yellow no. 10, FD&C green no.3

Disclaimer

*This product is not manufactured or distributed by Johnson & Johnson Healthcare Products, distributor of FreshBurst® ListerineAntiseptic Mouthwash.

Adverse reaction

DISTRIBUTED BY FOODHOLD, U.S.A., LLC

LANDOVER, MD 20785

1-844-846-9949

©2018 S&S Brands, LLC

Quality Guaranteed or Your Money Back.

DSP-TN-15000

DSP-MO-34

SDS-TN-15012

Principal display panel

careone®

Compare to FreshBurst® Listerine® Antiseptic Mouthwash*

ANTISEPTIC MOUTH RINSE

ANTIGINGIVITIS/ANTIPLAQUE

KILLS GERMS THAT CAUSE BAD BREATH, PLAQUE AND THE GUM DISEASE GINGIVITIS

SPRING MINT®FLAVOR

Sealed With Printed Neckband For Your Protection

16.9 FL OZ (500 mL)